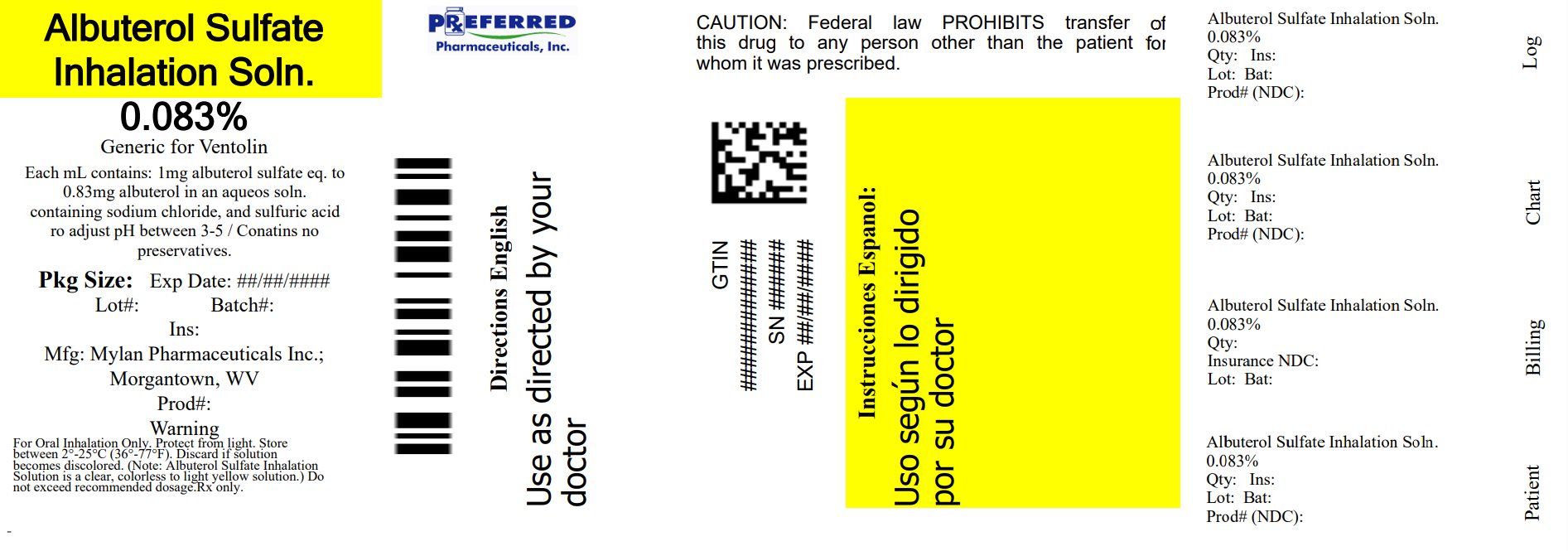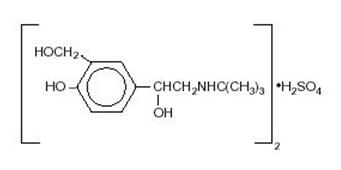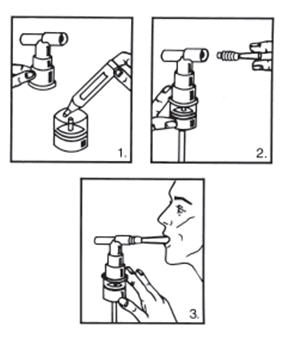 DRUG LABEL: Albuterol Sulfate
NDC: 68788-8399 | Form: SOLUTION
Manufacturer: Preferred Pharmaceuticals Inc.
Category: prescription | Type: HUMAN PRESCRIPTION DRUG LABEL
Date: 20260216

ACTIVE INGREDIENTS: Albuterol Sulfate 2.5 mg/3 mL
INACTIVE INGREDIENTS: Sodium Chloride; Sulfuric Acid; Water

Albuterol Sulfate Inhalation Solution 0.083% [(Potency expressed as albuterol, equivalent to 3 mg albuterol sulfate)]

PRESCRIBING INFORMATION

FOR INHALATION USE ONLY-NOT FOR INJECTION.

DESCRIPTION

Albuterol sulfate inhalation solution is a relatively selective beta2-adrenergic bronchodilator (see CLINICAL PHARMACOLOGY section below). Albuterol sulfate, the racemic form of albuterol, has the chemical name α^1-[(tert-Butylamino)methyl]-4-hydroxy-m-xylene-α,α'-diol sulfate (2:1) (salt), and the following structural formula:

Albuterol sulfate has a molecular weight of 576.70, and the molecular formula (C13H21NO3)2 • H2SO4. Albuterol sulfate is a white or practically white powder, freely soluble in water and slightly soluble in alcohol.

The World Health Organization recommended name for albuterol base is salbutamol.

Albuterol sulfate inhalation solution 0.083% requires no dilution before administration.

Each milliliter of Albuterol Sulfate Inhalation Solution 0.083% contains 0.83 mg of albuterol (as 1 mg of albuterol sulfate) in an isotonic, sterile, aqueous solution containing sodium chloride; sulfuric acid is used to adjust the pH to between 3 and 5. Albuterol Sulfate Inhalation Solution 0.083% contains no sulfiting agents or preservatives.

Albuterol sulfate inhalation solution is a clear, colorless to light yellow solution.

CLINICAL PHARMACOLOGY

The prime action of beta-adrenergic drugs is to stimulate adenyl cyclase, the enzyme which catalyzes the formation of cyclic-3',5'-adenosine monophosphate (cyclic AMP) from adenosine triphosphate (ATP). The cyclic AMP thus formed mediates the cellular responses. In vitro studies and in vivo pharmacologic studies have demonstrated that albuterol has a preferential effect on beta2-adrenergic receptors compared with isoproterenol. While it is recognized that beta2-adrenergic receptors are the predominant receptors in bronchial smooth muscle, 10% to 50% of the beta-receptors in the human heart may be beta2-receptors. The precise function of these receptors, however, is not yet established. Albuterol has been shown in most controlled clinical trials to have more effect on the respiratory tract in the form of bronchial smooth muscle relaxation than isoproterenol at comparable doses while producing fewer cardiovascular effects. Controlled clinical studies and other clinical experience have shown that inhaled albuterol, like other beta-adrenergic agonist drugs, can produce a significant cardiovascular effect in some patients, as measured by pulse rate, blood pressure, symptoms, and/or electrocardiographic changes.

Albuterol is longer acting than isoproterenol in most patients by any route of administration because it is not a substrate for the cellular uptake processes for catecholamines nor for catechol-O-methyl transferase.

Studies in asthmatic patients have shown that less than 20% of a single albuterol dose was absorbed following IPPB (intermittent positive-pressure breathing) or nebulizer administration; the remaining amount was recovered from the nebulizer and apparatus and expired air. Most of the absorbed dose was recovered in the urine 24 hours after drug administration. Following a 3 mg dose of nebulized albuterol, the maximum albuterol plasma level at 0.5 hour was 2.1 ng/mL (range 1.4 to 3.2 ng/mL). There was a significant dose-related response in FEV1 (forced expiratory volume in one second) and peak flow rate. It has been demonstrated that following oral administration of 4 mg albuterol, the elimination half-life was five to six hours.

Animal studies show that albuterol does not pass the blood-brain barrier. Recent studies in laboratory animals (minipigs, rodents, and dogs) recorded the occurrence of cardiac arrhythmias and sudden death (with histologic evidence of myocardial necrosis) when beta-agonists and methylxanthines were administered concurrently. The significance of these findings when applied to humans is currently unknown.

In controlled clinical trials, most patients exhibited an onset of improvement in pulmonary function within 5 minutes as determined by FEV1. FEV1 measurements also showed that the maximum average improvement in pulmonary function usually occurred at approximately 1 hour following inhalation of 2.5 mg of albuterol by compressor-nebulizer, and remained close to peak for 2 hours. Clinically significant improvement in pulmonary function (defined as maintenance of a 15% or more increase in FEV1 over baseline values) continued for 3 to 4 hours in most patients and in some patients continued up to 6 hours.

In repetitive dose studies, continued effectiveness was demonstrated throughout the three-month period of treatment in some patients.

Published reports of trials in asthmatic children aged 3 years or older have demonstrated significant improvement in either FEV1 or PEFR within 2 to 20 minutes following single doses of albuterol inhalation solution. An increase of 15% or more in baseline FEV1 has been observed in children aged 5 to 11 years up to 6 hours after treatment with doses of 0.10 mg/kg or higher of albuterol inhalation solution. Single doses of 3, 4, or 10 mg resulted in improvement in baseline PEFR that was comparable to extent and duration to a 2 mg dose, but doses above 3 mg were associated with heart rate increases of more than 10%.

INDICATIONS AND USAGE

Albuterol sulfate inhalation solution is indicated for the relief of bronchospasm in patients 2 years of age and older with reversible obstructive airway disease and acute attacks of bronchospasm.

CONTRAINDICATIONS

Albuterol sulfate inhalation solution is contraindicated in patients with a history of hypersensitivity to any of its components.

WARNINGS

As with other inhaled beta-adrenergic agonists, albuterol sulfate inhalation solution can produce paradoxical bronchospasm, which can be life threatening. If it occurs, the preparation should be discontinued immediately and alternative therapy instituted.

Fatalities have been reported in association with excessive use of inhaled sympathomimetic drugs and with the home use of nebulizers. It is, therefore, essential that the physician instruct the patient in the need for further evaluation, if his/her asthma becomes worse. In individual patients, any beta2-adrenergic agonist, including albuterol solution for inhalation, may have a clinically significant cardiac effect.

Immediate hypersensitivity reactions may occur after administration of albuterol as demonstrated by rare cases of urticaria, angioedema, rash, bronchospasm, and oropharyngeal edema.

PRECAUTIONS

General

Albuterol, as with all sympathomimetic amines, should be used with caution in patients with cardiovascular disorders, especially coronary insufficiency, cardiac arrhythmias and hypertension, in patients with convulsive disorders, hyperthyroidism or diabetes mellitus and in patients who are unusually responsive to sympathomimetic amines.

Large doses of intravenous albuterol have been reported to aggravate pre-existing diabetes mellitus and ketoacidosis. As with other beta-agonists, inhaled and intravenous albuterol may produce significant hypokalemia in some patients, possibly through intracellular shunting, which has the potential to produce adverse cardiovascular effects. The decrease is usually transient, not requiring supplementation.

Repeated dosing with 0.15 mg/kg of albuterol inhalation solution in children aged 5 to 17 years who were initially normokalemic has been associated with an asymptomatic decline of 20% to 25% in serum potassium levels.

Information for Patients

The action of albuterol sulfate inhalation solution may last up to six hours, and therefore it should not be used more frequently than recommended. Do not increase the dose or frequency of medication without medical consultation. If symptoms get worse, medical consultation should be sought promptly. While taking albuterol sulfate inhalation solution, other anti-asthma medicines should not be used unless prescribed.

Drug compatibility (physical and chemical), efficacy, and safety of albuterol sulfate inhalation solution when mixed with other drugs in a nebulizer have not been established.

See illustrated "Patient's Instructions for Use."

Drug Interactions

Other sympathomimetic aerosol bronchodilators or epinephrine should not be used concomitantly with albuterol.

Albuterol should be administered with extreme caution to patients being treated with monoamine oxidase inhibitors or tricyclic antidepressants, since the action of albuterol on the vascular system may be potentiated.

Beta-receptor blocking agents and albuterol inhibit the effect of each other.

Carcinogenesis, Mutagenesis, and Impairment of Fertility

Albuterol sulfate caused a significant dose-related increase in the incidence of benign leiomyomas of the mesovarium in a 2-year study in the rat, at oral doses of 2, 10, and 50 mg/kg, corresponding to 10, 50 and 250 times, respectively, the maximum nebulization dose for a 50 kg human. In another study this effect was blocked by the coadministration of propranolol. The relevance of these findings to humans is not known. An 18-month study in mice and a lifetime study in hamsters revealed no evidence of tumorigenicity. Studies with albuterol revealed no evidence of mutagenesis. Reproduction studies in rats revealed no evidence of impaired fertility.

Pregnancy

Teratogenic Effects

Pregnancy Category C

Albuterol has been shown to be teratogenic in mice when given subcutaneously in doses corresponding to 1.25 times the human nebulization dose (based on a 50 kg human). There are no adequate and well-controlled studies in pregnant women. Albuterol should be used during pregnancy only if the potential benefit justifies the potential risk to the fetus. A reproduction study in CD-1 mice with albuterol (0.025, 0.25, and 2.5 mg/kg subcutaneously, corresponding to 0.125, 1.25 and 12.5 times the maximum human nebulization dose, respectively) showed cleft palate formation in 5 of 111 (4.5%) fetuses at 0.25 mg/kg and in 10 of 108 (9.3%) fetuses at 2.5 mg/kg. None were observed at 0.025 mg/kg. Cleft palate also occurred in 22 of 72 (30.5%) fetuses from females treated with 2.5 mg/kg isoproterenol (positive control). A reproduction study in Stride Dutch rabbits revealed cranioschisis in 7 of 19 (37%) fetuses at 50 mg/kg, corresponding to 250 times the maximum nebulization dose for a 50 kg human.

During worldwide marketing experience, various congenital anomalies, including cleft palate and limb defects, have been rarely reported in the offspring of patients being treated with albuterol. Some of the mothers were taking multiple medications during their pregnancies. No consistent pattern of defects can be discerned, and a relationship between albuterol use and congenital anomalies has not been established.

Labor and Delivery

Oral albuterol has been shown to delay preterm labor in some reports. There are presently no well-controlled studies that demonstrate that it will stop preterm labor or prevent labor at term. Therefore, cautious use of albuterol sulfate inhalation solution is required in pregnant patients when given for relief of bronchospasm so as to avoid interference with uterine contractibility.

Nursing Mothers

It is not known whether this drug is excreted in human milk. Because of the potential for tumorigenicity shown for albuterol in some animal studies, a decision should be made whether to discontinue nursing or to discontinue the drug, taking into account the importance of the drug to the mother.

Pediatric Use

The safety and effectiveness of albuterol sulfate inhalation solution have been established in children 2 years of age or older. Use of albuterol sulfate inhalation solution in these age-groups is supported by evidence from adequate and well-controlled studies of albuterol sulfate inhalation solution in adults; the likelihood that the disease course, pathophysiology, and the drug's effect in pediatric and adult patients are substantially similar; and published reports of trials in pediatric patients 3 years of age or older. The recommended dose for the pediatric population is based upon three published dose comparison studies of efficacy and safety in children aged 5 to 17 years, and on the safety profile in both adults and pediatric patients at doses equal to or higher than the recommended doses. The safety and effectiveness of albuterol sulfate inhalation solution in children below 2 years of age have not been established.

ADVERSE REACTIONS

Clinical Trial Experience

The results of clinical trials with albuterol sulfate inhalation solution in 135 patients showed the following side effects which were considered probably or possibly drug related:

Central Nervous System: tremors (20%), dizziness (7%), nervousness (4%), headache (3%), insomnia (1%).

Gastrointestinal: nausea (4%), dyspepsia (1%).

Ear, Nose, and Throat: pharyngitis (<1%), nasal congestion (1%).

Cardiovascular: tachycardia (1%), hypertension (1%).

Respiratory: bronchospasm (8%), cough (4%), bronchitis (4%), wheezing (1%).

No clinically relevant laboratory abnormalities related to albuterol sulfate inhalation solution administration were determined in these studies.

In comparing the adverse reactions reported for patients treated with albuterol sulfate inhalation solution with those of patients treated with isoproterenol during clinical trials of three months, the following moderate to severe reactions, as judged by the investigators, were reported. This table does not include mild reactions.

Percent Incidence of Moderate to Severe Adverse Reactions
Reaction | Albuterol N=65 | Isoproterenol N=65
Central Nervous System
Tremors | 10.7% | 13.8%
Headache | 3.1% | 1.5%
Insomnia | 3.1% | 1.5%
Cardiovascular
Hypertension | 3.1% | 3.1%
Arrhythmias | 0% | 3%
[The finding of no arrhythmias and no palpitations after albuterol administration in this clinical study should not be interpreted as indicating that these adverse effects cannot occur after the administration of inhaled albuterol.] Palpitation | 0% | 22%
Respiratory
[In most cases of bronchospasm, this term was generally used to describe exacerbations in the underlying pulmonary disease.] Bronchospasm | 15.4% | 18%
Cough | 3.1% | 5%
Bronchitis | 1.5% | 5%
Wheeze | 1.5% | 1.5%
Sputum Increase | 1.5% | 1.5%
Dyspnea | 1.5% | 1.5%
Gastrointestinal
Nausea | 3.1% | 0%
Dyspepsia | 1.5% | 0%
Systemic
Malaise | 1.5% | 0%

Post-Marketing Experience

Cases of urticaria, angioedema, rash, bronchospasm, hoarseness, oropharyngeal edema, arrhythmias (including atrial fibrillations, supraventricular tachycardia, extrasystoles) and metabolic acidosis have been reported after the use of albuterol sulfate inhalation solution. Because these reactions are reported voluntarily from a population of uncertain size, it is not always possible to reliably estimate their frequency or establish a casual relationship to drug exposure.

OVERDOSAGE

Manifestations of overdosage may include seizures, anginal pain, hypertension, hypokalemia, tachycardia with rates up to 200 beats/min, and exaggeration of the pharmacological effects listed in . In isolated cases in children 2 to 12 years of age, tachycardia with rates >200 beats/min has been observed.

The oral LD50 in rats and mice was greater than 2,000 mg/kg. The inhalational LD50 could not be determined.

There is insufficient evidence to determine if dialysis is beneficial for overdosage of albuterol inhalation solution.

DOSAGE AND ADMINISTRATION

Adults and Children 2 to 12 Years of Age

The usual dosage for adults and for children weighing at least 15 kg is 2.5 mg of albuterol (one vial) administered three to four times daily by nebulization. Children weighing < 15 kg who require < 2.5 mg/dose (i.e., less than a full vial) should use albuterol inhalation solution, 0.5% instead of albuterol inhalation solution, 0.083%. More frequent administration or higher doses are not recommended. To administer 2.5 mg of albuterol, administer the entire contents of one sterile unit dose vial (3 mL of 0.083% inhalation solution) by nebulization. The flow rate is regulated to suit the particular nebulizer so that albuterol inhalation solution will be delivered over approximately 5 to 15 minutes.

The use of albuterol sulfate inhalation solution can be continued as medically indicated to control recurring bouts of bronchospasm. During this time most patients gain optimum benefit from regular use of the inhalation solution.

If a previously effective dosage regimen fails to provide the usual relief, medical advice should be sought immediately, as this is often a sign of seriously worsening asthma which would require reassessment of therapy.

HOW SUPPLIED

Unit-dose plastic vial containing Albuterol Sulfate Inhalation Solution 0.083%, 2.5 mg/3 mL [(Potency expressed as albuterol, equivalent to 3 mg albuterol sulfate)] . Equivalent to 0.5 mL albuterol (as the sulfate) 0.5% (2.5 mg albuterol) diluted to 3 mL. Supplied in cartons as listed below.

NDC 68788-8399-2 25 vials per carton / 25 vials per foil pouch

Storage

PROTECT FROM LIGHT. Store in pouch until time of use. Store between 2° and 25° C (36° and 77° F).

Rx only.

Manufactured for:
Mylan Pharmaceuticals Inc.
Morgantown, WV 26505
Manufactured by:
The Ritedose Corporation
Columbia, SC 29203

TRC:ALSUIS:R3

JAN 2013

PATIENT'S INSTRUCTIONS FOR USE

Albuterol Sulfate Inhalation Solution 0.083% [(Potency expressed as albuterol, equivalent to 3 mg albuterol sulfate).]

Note: This is a unit-dose vial. No dilution is required.

Read complete instructions carefully before using.

1. Remove the vial from the foil pouch.
2. Twist the cap completely off the vial and squeeze the contents into the nebulizer reservoir (Figure 1).
3. Connect the nebulizer reservoir to the mouthpiece or face mask (Figure 2).
4. Connect the nebulizer to the compressor.
5. Sit in a comfortable, upright position; place the mouthpiece in your mouth (Figure 3)(or put on the face mask); and turn on the compressor.
6. Breathe as calmly, deeply and evenly as possible until no more mist is formed in the nebulizer chamber (about 5 to 15 minutes). At this point, the treatment is finished.
7. Clean the nebulizer (see manufacturer's instructions).

Note: Use only as directed by your physician. More frequent administration or higher doses are not recommended.

Store Albuterol Sulfate Inhalation Solution 0.083% between 2° and 25° C (36° and 77° F). Store in pouch until time of use.

ADDITIONAL INSTRUCTIONS: ___________________________________________
________________________________________________________________________
________________________________________________________________________

Manufactured for:
Mylan Pharmaceuticals Inc.
Morgantown, WV 26505
Manufactured by:
The Ritedose Corporation
Columbia, SC 29203

TRC:PIL:ALSUIS:R3

JAN 2013

Relabeled By: Preferred Pharmaceuticals Inc.

PRINCIPAL DISPLAY PANEL - 25 x 3 mL Vials Carton

Mylan®

NDC 68788-8399-2

Relabeled By: Preferred Pharmaceuticals Inc.

Albuterol Sulfate
Inhalation Solution, 0.083%*

2.5 mg / 3 mL*

*Potency expressed as albuterol, equivalent to 3 mg albuterol sulfate.

FOR ORAL INHALATION ONLY

Each mL contains 1 mg albuterol sulfate, equivalent to 0.83 mg albuterol
in an aqueous solution containing sodium chloride and sulfuric acid
to adjust pH between 3 and 5. Contains no preservatives.
Please consult your physician before use. Do not exceed recommended dosage.
Usual Dosage: See package insert. Protect from light.
Store between 2° and 25°C (36° and 77°F). Discard if solution becomes discolored.
(Note: Albuterol Sulfate Inhalation Solution is a clear, colorless to light yellow solution.)

Rx only

25 x 3 mL Sterile Unit-Dose Vials

Equivalent to 0.5 mL Albuterol Sulfate 0.5%* diluted to 3 mL
with normal saline.

Attention Pharmacist: Detach "Patient's Instructions For Use"
from package insert and dispense with solution.

Protect from light. Store between 2° and 25°C (36° and 77°F).
Discard if solution becomes discolored.

(Note: Albuterol Sulfate Inhalation Solution is a clear,
colorless to light yellow solution.)

Manufactured for:
Mylan Pharmaceuticals Inc.
Morgantown, WV 26505

Manufactured by:
The Ritedose Corporation
Columbia, SC 29203

Relabeled By: Preferred Pharmaceuticals Inc.

TRC:8270:25C:R2